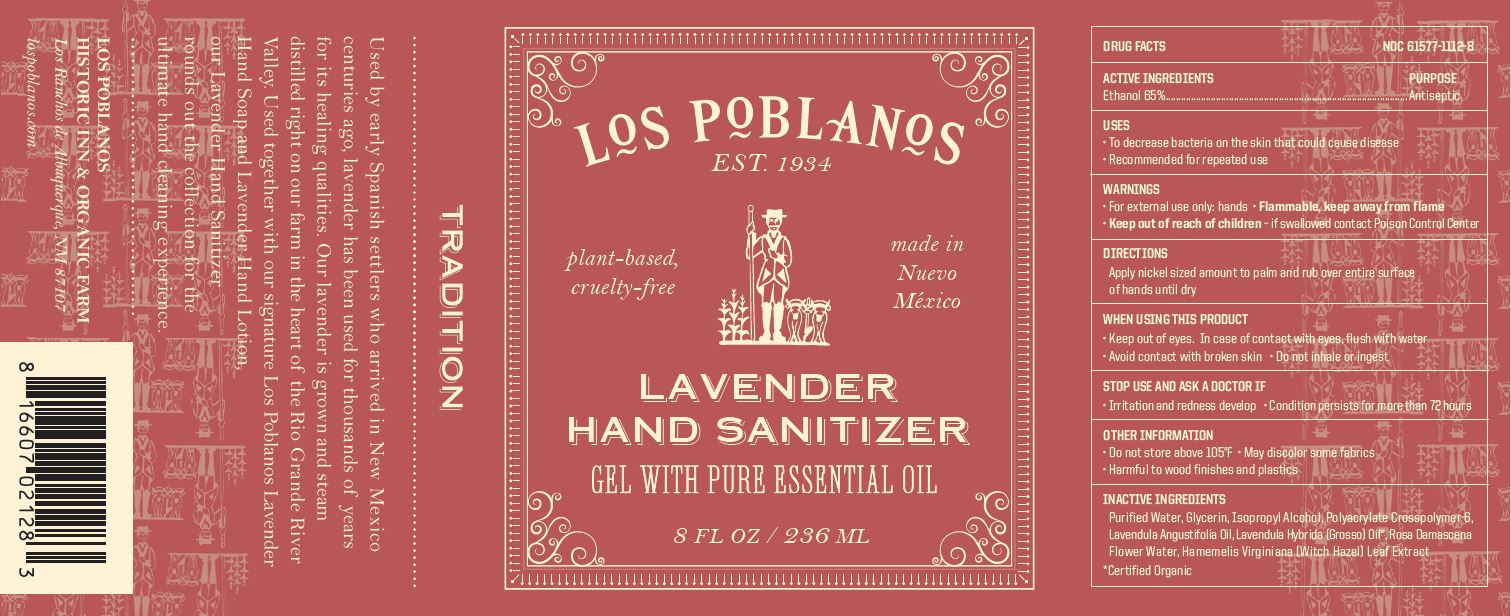 DRUG LABEL: LOS POBLANOS LAVENDER HAND SANITIZER
NDC: 61577-1112 | Form: GEL
Manufacturer: SOMBRA COSMETICS
Category: otc | Type: HUMAN OTC DRUG LABEL
Date: 20200715

ACTIVE INGREDIENTS: ALCOHOL 65 mL/100 mL
INACTIVE INGREDIENTS: WATER; GLYCERIN; ISOPROPYL ALCOHOL; LAVANDULA ANGUSTIFOLIA FLOWER; LAVANDIN OIL; AMMONIUM ACRYLOYLDIMETHYLTAURATE, DIMETHYLACRYLAMIDE, LAURYL METHACRYLATE AND LAURETH-4 METHACRYLATE COPOLYMER, TRIMETHYLOLPROPANE TRIACRYLATE CROSSLINKED (45000 MPA.S); ROSA DAMASCENA FLOWER; WITCH HAZEL

Los Poblanos Lavender Hand Sanitizer

Active Ingredients

Ethyl Alcohol 65%

Uses

Helps reduce bacteria on the skin that could cause diseases.

Warnings

Flammable. Keep away from fire or flame. For external use only.

Do not use

When using this product, do not use in or near the eyes. In case of contact, rinse eyes thoroughly with water.

When Using

When using this product, do not use in or near the eyes. In case of contact, rinse eyes thoroughly with water.

Stop use and ask a doctor if irritation or rash appears and lasts.

Keep out of reach of children. If swallowed, get medical help or contact a Poison Control Center right away.

Directions

Place enough product in the palm of your hands to thoroughly cover your hands. Rub hands together briskly until product is completely absorbed and hands are dry.

Other information

Store between 15-30C (59-86F)
Avoid freezing and excessive heat above 40C (105F)

Inactive ingredients

glycerin, purified water, isopropyl alcohol, polyacrylate crosspolymer-6, lavandula angustifolia oil, lavandula hybrida (grosso) oil*, rosa damascena flower water, hamamelis virginiana (witch hazel) leaf extract

*organic

Purpose

Antiseptic, Hand Sanitizer